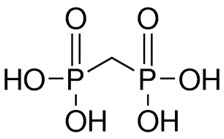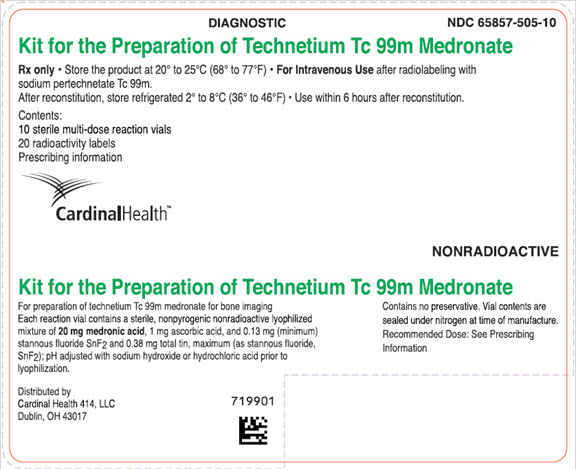 DRUG LABEL: Kit for the Preparation of Technetium Tc 99m Medronate
NDC: 65857-505 | Form: INJECTION, POWDER, LYOPHILIZED, FOR SOLUTION
Manufacturer: Cardinal Health 414, LLC
Category: prescription | Type: HUMAN PRESCRIPTION DRUG LABEL
Date: 20250908

ACTIVE INGREDIENTS: TECHNETIUM TC-99M MEDRONATE 20 mg/1 1
INACTIVE INGREDIENTS: ASCORBIC ACID; STANNOUS FLUORIDE; SODIUM HYDROXIDE; HYDROCHLORIC ACID

Kit for the Preparation of Technetium Tc 99m Medronate
For Diagnostic Use

DESCRIPTION

Each reaction vial contains a sterile, nonpyrogenic, nonradioactive lyophilized mixture of 20 mg medronic acid, 1 mg ascorbic acid, 0.13 mg (minimum) stannous fluoride, SnF2 and 0.38 mg total tin, maximum (as stannous fluoride, SnF2).

The pH is adjusted with sodium hydroxide or hydrochloric acid to 6.5 (6.3 to 6.7) prior to lyophilization. The vial does not contain a preservative. The contents of the vial are lyophilized and sealed under nitrogen at the time of manufacture.

The pH of the reconstituted product is 5.4 to 6.8.

The structure of medronic acid is given below:

The precise structure of technetium Tc 99m medronate is unknown at this time.

When sterile, pyrogen-free sodium pertechnetate Tc 99m injection is added to the vial, the diagnostic agent technetium Tc 99m medronate is formed for administration by intravenous injection.

PHYSICAL CHARACTERISTICS

Technetium Tc 99m decays by isomeric transition with a physical half-life of 6.02 hours.^1 The principal photon that is useful for detection and imaging studies is shown in Table 1.

Table 1
Principal Radiation Emission Data
Radiation | Mean % per Disintegration | Mean Energy (keV)
Gamma-2 | 89.07 | 140.5
^1 Kocher, David C: Radioactive Decay Data Tables, DOE/TlC-11026, 108, 1981

External Radiation

The specific gamma ray constant for Tc 99m is 0.78 R/ hour-millicurie at 1 cm. The first half-value layer is 0.017 cm lead (Pb). A range of values for the relative attenuation of the radiation emitted by this radionuclide that results from interposition of various thicknesses of Pb is shown in Table 2. To facilitate control of the radiation exposure from millicurie amounts of this radionuclide, the use of a 0.25 cm thickness of Pb will attenuate the radiation emitted by a factor of about 1,000.

Table 2
Radiation Attenuation by Lead Shielding
Shield Thickness (Pb) cm | Coefficient of Attenuation
0.017 | 0.5
0.08 | 10^-1
0.16 | 10^-2
0.25 | 10^-3
0.33 | 10^-4

To correct for physical decay of technetium Tc 99m, the fractions that remain at selected intervals after the time of calibration are shown in Table 3.

Table 3
Physical Decay Chart: Tc 99m, half-life 6.02 hours
Hours | Fraction Remaining | Hours | Fraction Remaining
0* | 100.0 | 7 | 0.447
1 | 0.891 | 8 | 0.398
2 | 0.794 | 9 | 0.355
3 | 0.708 | 10 | 0.316
4 | 0.631 | 11 | 0.282
5 | 0.562 | 12 | 0.251
6 | 0.501
* Calibration Time

CLINICAL PHARMACOLOGY

During the initial 24 hours following intravenous injection of technetium Tc 99m medronate, about 50 percent of the dose is retained in the skeleton, and about 50 percent is excreted in the urine. A minimum amount of uptake has been observed in soft-tissue organs, most notably the kidneys.

Clearance of radioactivity from the blood is quite rapid, with about 10 percent of the injected dose remaining at one hour, and less than 5 and 2 percent at two and four hours, respectively. The rapid blood clearance (T ½: 38 to 75 minutes) provides bone to non-osseous tissue ratios favoring early imaging.

Following intravenous administration of technetium Tc 99m medronate, skeletal uptake occurs as a function of blood flow to bone and bone efficiency in extracting the complex. Bone mineral crystals are generally considered to be hydroxyapatite, and the complex appears to have an affinity for the hydroxyapatite crystals in bone.

Deposition of radioactivity in bone is rapid and appears to be related to osteogenic activity as well as the aforementioned skeletal blood perfusion. Skeletal uptake is bilaterally uniform, with larger concentrations in the axial structure and in the long bones. Increased accumulation of radioactivity may be seen, generally, in any bone disease state in which there is increased osteogenesis or a localized increase in osseous blood perfusion; consequently, bone imaging agents generally are not effective in detecting chronic bone diseases.

INDICATIONS AND USAGE

Technetium Tc 99m medronate may be used as a bone imaging agent to delineate areas of altered osteogenesis.

CONTRAINDICATIONS

None known.

WARNINGS

This class of compounds is known to complex cations such as calcium. Particular caution should be used with patients who have or who may be predisposed to hypocalcemia (i.e., alkalosis).

Preliminary reports indicate interference with brain scans using sodium pertechnetate Tc 99m injection which have been preceded by a bone scan using an agent containing stannous ions. This interference may result in false-positive or false-negative brain scans. It is recommended, where feasible, that brain scans precede bone imaging procedures.

The biodistribution of technetium Tc 99m medronate may be altered in the presence of high levels of certain cations (iron, calcium, and aluminum). This may result in reduced uptake of radionuclide in the skeleton and increased extraosseal uptake, which may potentially degrade imaging quality. High levels of these cations may be caused by concomitant medications or medical conditions (e.g., iron overload, hypercalcemia, etc.). Most cases were observed after iron infusion. (See PRECAUTIONS, Drug Interactions.)

PRECAUTIONS

General

The contents of the kit before preparation are not radioactive. However, after the sodium pertechnetate Tc 99m injection is added, adequate shielding of the final preparation must be maintained.

Contents of the reaction vial are intended only for use in the preparation of technetium Tc 99m medronate and are NOT to be administered directly to the patient.

Technetium Tc 99m medronate as well as other radioactive drugs, must be handled with care. Once sodium pertechnetate Tc 99m is added to the vial, appropriate safety measures should be used to minimize external radiation to clinical occupational personnel. Care should also be taken to minimize radiation exposure to patients in a manner consistent with proper patient management.

To minimize the radiation dose to the bladder, the patient should be encouraged to drink fluids and to void immediately before the examination and as often thereafter as possible for the next four to six hours.

Technetium Tc 99m medronate should be formulated within six (6) hours prior to clinical use. Optimal imaging results are obtained one to four hours after administration. Technetium Tc 99m medronate injection should be discarded six hours after reconstitution. The solution should not be used if cloudy.

The components of the kit are sterile and pyrogen-free. It is essential to follow directions carefully and to adhere to strict aseptic procedures during preparation.

The technetium Tc 99m labeling reactions involved in preparing the agent depend on maintaining the stannous ion in the reduced state. Any oxidant present in the sodium pertechnetate Tc 99m supply may, thus, adversely affect the quality of the radiopharmaceutical. Hence, sodium pertechnetate Tc 99m containing oxidants should not be employed.

Radiopharmaceuticals should be used only by physicians who are qualified by training and experience in the safe use and handling of radionuclides.

Drug Interactions

The biodistribution of technetium Tc 99m medronate may be altered in the presence of high levels of certain cations (iron, calcium, and aluminum). This may result in reduced uptake of radionuclide in the skeleton and increased extraosseal uptake, which may potentially degrade imaging quality. In patients with high levels of these cations caused by concomitant medications, particularly patients receiving iron infusions, consider performing an imaging study with technetium Tc 99m medronate injection once the cation levels have normalized (e.g., after 3 to 5 half-lives of the cation). (See WARNINGS.)

Carcinogenesis, Mutagenesis, Impairment of Fertility

No long-term animal studies have been performed to evaluate carcinogenic potential or whether technetium Tc 99m medronate affects fertility in males or females.

Pregnancy

Animal reproduction studies have not been conducted with technetium Tc 99m medronate. It is also not known whether technetium Tc 99m medronate can cause fetal harm when administered to a pregnant woman or can affect reproductive capacity. Technetium Tc 99m medronate should be given to a pregnant woman only if clearly needed.

Nursing Mothers

Technetium Tc 99m is excreted in human milk during lactation; therefore, formula-feedings should be substituted for breast-feedings.

Pediatric Use

Safety and effectiveness in children have not been established.

ADVERSE REACTIONS

Several adverse reactions due to technetium Tc 99m medronate have been reported. These were usually hypersensitivity reactions characterized by itching, various skin rashes, hypotension, chills, nausea and vomiting. There have also been rare cases of dizziness and asthenia associated with the use of technetium Tc 99m medronate.

DOSAGE AND ADMINISTRATION

After preparation with oxidant-free sodium pertechnetate Tc 99m injection the suggested dose range of technetium Tc 99m medronate injection in the average patient (70 kg) is 370 MBq to 740 MBq (10 mCi to 20 mCi) given intravenously. Imaging post injection is optimal at 1 to 4 hours.

The patient dose should be measured by a suitable radioactivity calibration system immediately prior to administration.

Parenteral drug products should be inspected visually for particulate matter and discoloration prior to administration whenever solution and container permit. Shielding should be utilized when preparing the technetium Tc 99m medronate injection.

Radiation Dosimetry

The effective half-life was assumed to be the physical half-life for all calculated values. The estimated radiation absorbed doses to an average patient (70 kg) from an intravenous injection of a maximum dose of 740 MBq (20 mCi) of technetium Tc 99m medronate are shown in Table 4.

Table 4
Absorbed Radiation Dose
Organ |  | mGy/740 MBq | rads/20 mCi
Total Body |  | 1.3 | 0.13
Bone Total |  | 7.0 | 0.70
Red Marrow |  | 5.6 | 0.56
Kidneys |  | 8.0 | 0.80
Liver |  | 0.6 | 0.06
Bladder Wall | 2-hr. void | 26.0 | 2.60
 | 4.8-hr. void | 62.0 | 6.20
Ovaries | 2-hr. void | 2.4 | 0.24
 | 4.8-hr. void | 3.4 | 0.34
Testes | 2-hr. void | 1.6 | 0.16
 | 4.8-hr. void | 2.2 | 0.22

Method of Calculation: “S” Absorbed Dose per Unit Cumulated Activity for Selected Radionuclides and Organs, MIRD Pamphlet No. 11, 1975

HOW SUPPLIED

Kit for the Preparation of Technetium Tc 99m Medronate is supplied as kits of 10 reaction vials (NDC 65857-505-10).

Each reaction vial contains a sterile, nonpyrogenic, nonradioactive lyophilized mixture of 20 mg medronic acid, 1 mg ascorbic acid, 0.13 mg (minimum) stannous fluoride, SnF2 and 0.38 mg total tin, maximum (as stannous fluoride, SnF2).

The pH is adjusted with sodium hydroxide or hydrochloric acid prior to lyophilization. The vial does not contain a preservative. The contents of the vial are lyophilized and sealed under nitrogen at the time of manufacture. The pH of the reconstituted product is 5.4 to 6.8.

Kit Contents
10 sterile reaction vials
20 pressure-sensitive labels for technetium Tc 99m medronate
1 package insert

Storage

Store the product as supplied at 20° to 25°C (68° to 77°F). After reconstitution store refrigerated at 2° to 8°C (36° to 46°F).

Do not use and discard radiolabeled technetium Tc 99m medronate 6 hours after reconstitution.

DIRECTIONS FOR PREPARATION OF TECHNETIUM Tc 99m MEDRONATE

Procedural Precautions

The lyophilized powder in the reaction vial is sterile and nonpyrogenic and does not contain a preservative. Aseptic procedure and shielded syringes should be used when adding the pertechnetate eluate to the reaction vial and for withdrawal and administration of the dose of the finished medronate agent. Waterproof gloves should be worn to prevent the possibility of radioactive contamination of the hands.

If sodium pertechnetate Tc 99m must be diluted prior to injection into the reaction vial, only preservative-free 0.9% Sodium Chloride Injection USP should be used.

Preparation

Preparation of technetium Tc 99m medronate is done by the following aseptic procedure:

1. Waterproof gloves should be worn during the preparation procedure.
2. Place reaction vial in an appropriate lead shield.
3. Remove the central disc from the reaction vial and swab the rubber closure of the reaction vial with a germicide.
4. With a sterile syringe, aseptically obtain 0.5 mL to 5 mL [up to 18,500 MBq (500 mCi)] of a suitable, oxidant-free, sterile nonpyrogenic sodium pertechnetate.
5. Aseptically add the sodium pertechnetate Tc 99m solution to the vial.
6. Secure the lead shield cover. Swirl the vial for one minute and let stand for one to two minutes.
7. Record the date and time of preparation on pressure-sensitive label.
8. Affix pressure-sensitive label to shield.
9. Examine vial contents. If the solution is not clear and free of particulate matter and discoloration on visual inspection, it should not be used.
10. Measure the radioactivity using a suitable calibration system and record on the shield label prior to patient administration.
11. Aseptically withdraw material for use within six (6) hours of preparation. For optimum results, this time should be minimized. The vial contains no bacteriostatic preservative.

The U.S. Nuclear Regulatory Commission has approved this reagent kit for distribution to persons licensed to use byproduct material identified in §35.200 of 10 CFR Part 35, to persons who hold an equivalent license issued by an Agreement State, and, outside the United States, to persons authorized by the appropriate authority.

Distributed by:
Cardinal Health 414, LLC
Dublin, OH 43017

Revised February 2025

PRINCIPAL DISPLAY PANEL - Carton Label

Carton Label

DIAGNOSTIC

NDC 65857-505-10

Kit for the Preparation of Technetium Tc 99m Medronate

Rx only • Store the product at 20° to 25°C (68° to 77°F) • For Intravenous Use after radiolabeling with
sodium pertechnetate Tc 99m.
After reconstitution, store refrigerated 2° to 8°C (36° to 46°F) • Use within 6 hours after reconstitution.

Contents:
10 sterile multi-dose reaction vials
20 radioactivity labels
Prescribing information

CardinalHealth™

NONRADIOACTIVE

Kit for the Preparation of Technetium Tc 99m Medronate

For preparation of technetium Tc 99m medronate for bone imaging
Each reaction vial contains a sterile, nonpyrogenic nonradioactive lyophilized
mixture of 20 mg medronic acid, 1 mg ascorbic acid, and 0.13 mg (minimum)
stannous fluoride SnF2 and 0.38 mg total tin, maximum (as stannous fluoride,
SnF2); pH adjusted with sodium hydroxide or hydrochloric acid prior to
lyophilization.

Distributed by
Cardinal Health 414, LLC
Dublin, OH 43017

Contains no preservative. Vial contents are
sealed under nitrogen at time of manufacture.
Recommended Dose: See Prescribing
Information.